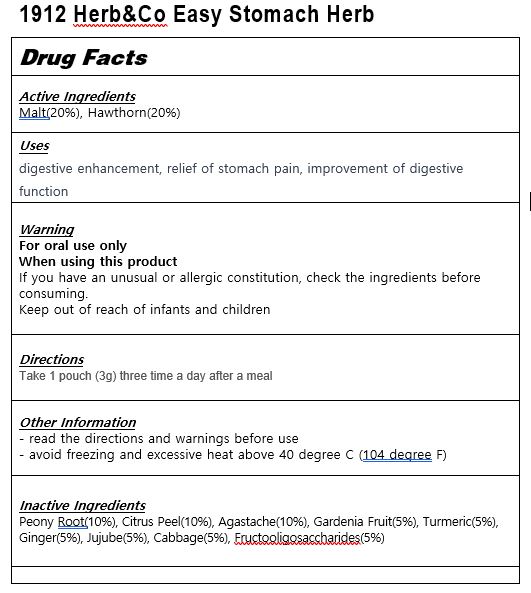 DRUG LABEL: 1912 Herb Co Easy Stomach Herb
NDC: 83933-0002 | Form: POWDER
Manufacturer: Agricultural Corporation YUBIMUHUAN CO Ltd
Category: otc | Type: HUMAN OTC DRUG LABEL
Date: 20240102

ACTIVE INGREDIENTS: HAWTHORN LEAF WITH FLOWER 20 g/100 g
INACTIVE INGREDIENTS: PAEONIA LACTIFLORA ROOT

Drug Facts

ACTIVE INGREDIENT

Malt(20%), Hawthorn(20%)

INACTIVE INGREDIENT

Peony Root(10%), Citrus Peel(10%), Agastache(10%), Gardenia Fruit(5%), Turmeric(5%), Ginger(5%), Jujube(5%), Cabbage(5%), Fructooligosaccharides(5%)

PURPOSE

digestive enhancement, relief of stomach pain, improvement of digestive function

keep out of reach of the children

INDICATIONS AND USAGE

Take 1 pouch (3g) three time a day after a meal

WARNINGS

If you have an unusual or allergic constitution, check the ingredients before consuming.

DOSAGE AND ADMINISTRATION

for oral use only